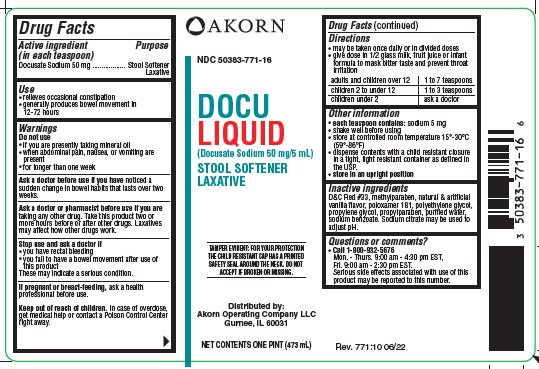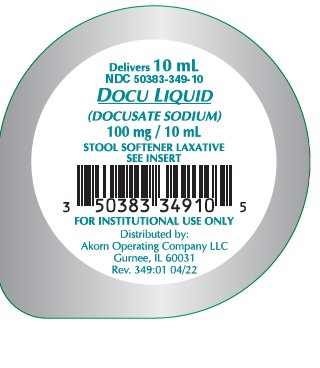 DRUG LABEL: Docu Liquid
NDC: 50383-771 | Form: LIQUID
Manufacturer: Akorn Operating Company LLC
Category: otc | Type: HUMAN OTC DRUG LABEL
Date: 20221013

ACTIVE INGREDIENTS: DOCUSATE SODIUM 50 mg/5 mL
INACTIVE INGREDIENTS: D&C RED NO. 33; METHYLPARABEN; POLYETHYLENE GLYCOL 400; PROPYLENE GLYCOL; PROPYLPARABEN; SODIUM BENZOATE; SODIUM CITRATE, UNSPECIFIED FORM; WATER; POLOXAMER 181

Drug Facts

Active ingredient

Docusate Sodium 50 mg

Purpose

Stool Softener Laxative

Uses

- relieves occasional constipation
- generally produces bowel movement in 12-72

Warnings

Do Not Use

- if you are presently taking mineral oil
- when abdominal pain, nausea, or vomiting are present
- for longer than one week

Ask a doctor before use if you have

noticed a sudden change in bowel habits that lasts over two weeks.

Ask a doctor or pharmacist before use if you are

taking any other drug. Take this product two or more hours before or after other drugs. Laxatives may affect how other drugs work.

Stop use and ask a doctor if

- you have rectal bleeding
- you fail to have a bowel movement after use of this product

These may indicate a serious condition.

If pregnant or breast-feeding,

ask a health professional before use.

Keep Out of Reach of Children

In case of overdose, get medical help or contact a Poison Control Center right away.

Directions

- may be taken once daily or in divided doses
- give dose in 1/2 glass of milk, fruit juice or infant formula to mask bitter taste and prevent throat irritation

adults and children over 12 | 1 to 7 teaspoons
children 2 to under 12 | 1 to 3 teaspoons
children under 2 | ask a doctor

Other information

- each teaspoon contains: sodium 5 mg
- shake well before using
- store at controlled room temperature 15° - 30°C (59° - 86°F)
- dispense contents with a child resistant closure in a tight, light resistant container as defined in the USP
- store in an upright position

Inactive Ingredients

D&C Red #33, methylparaben, natural & artificial vanilla flavor, poloxamer 181, polyethylene glycol, propylene glycol, propylparaben, purified water, sodium benzoate. Sodium citrate may be used to adjust pH.

Questions or comments?

- Call 1-800-932-5676

Mon - Thurs. 9:00 am - 4:30 pm EST, Fri. 9:00 am - 2:30 pm EST.

Serious side effects associated with use of this product may be reported to this number.

Package/Label Principal Display Panel

NDC 50383-771-16

DOCU LIQUID

(Docusate Sodium 50 mg/5 mL)

STOOL SOFTENER LAXATIVE

TAMPER EVIDENT: FOR YOUR PROTECTION THE CHILD RESISTANT CAP HAS A PRINTED SAFETY SEAL AROUND THE NECK. DO NOT ACCEPT IF BROKEN OR MISSING.

Distributed by:

Akorn Operating Company LLC

Gurnee, IL 60031

NET CONTENTS ONE PINT (473 mL)

Package/Label Principal Display Panel

Delivers 10 mL

NDC 50383-349-10

DOCU LIQUID

(DOCUSATE SODIUM)

100 mg/ 10 mL

STOOL SOFTENER LAXATIVE

SEE INSERT

Barcode 3 5038334910 5

FOR INSTITUTIONAL USE ONLY

Distributed by:

Akorn Operating Company LLC

Gurnee, IL 60031

Rev. 349:01 04/22